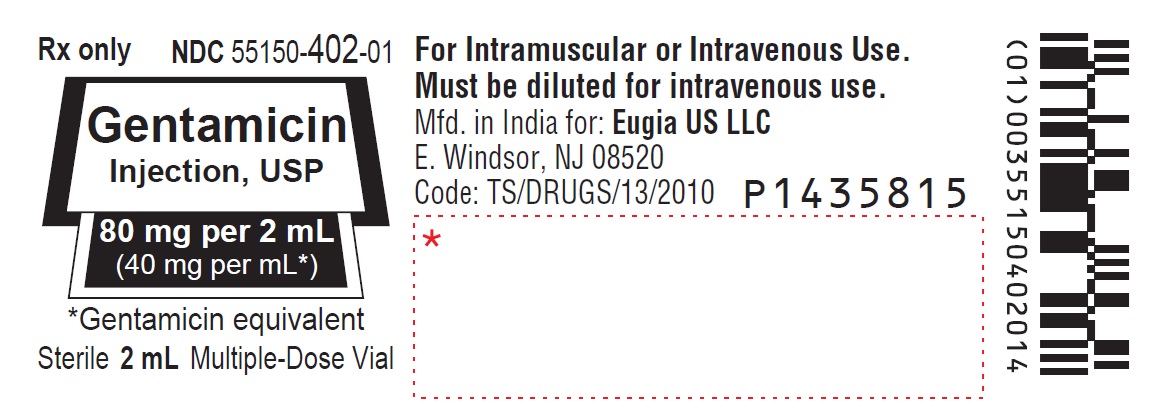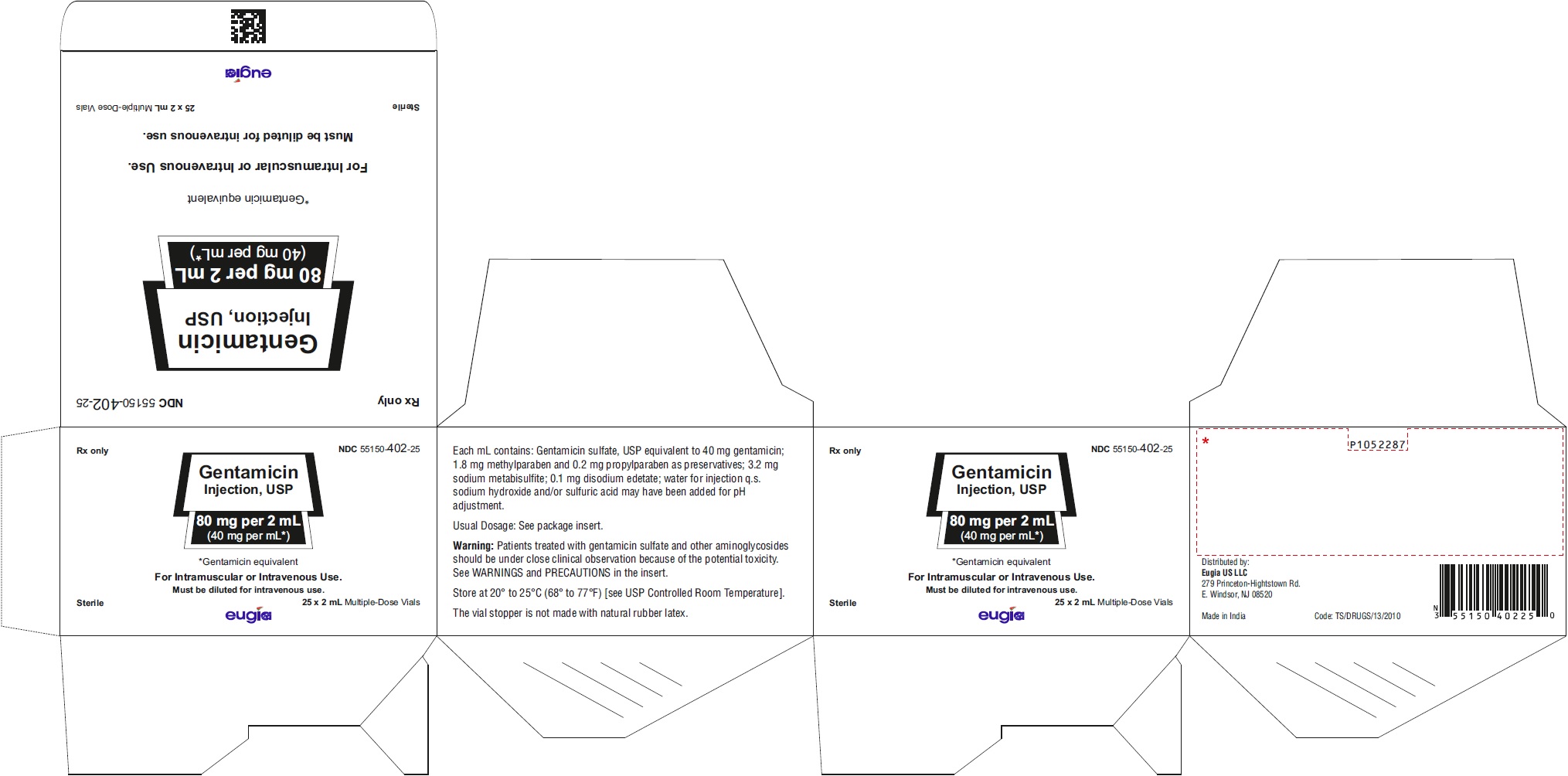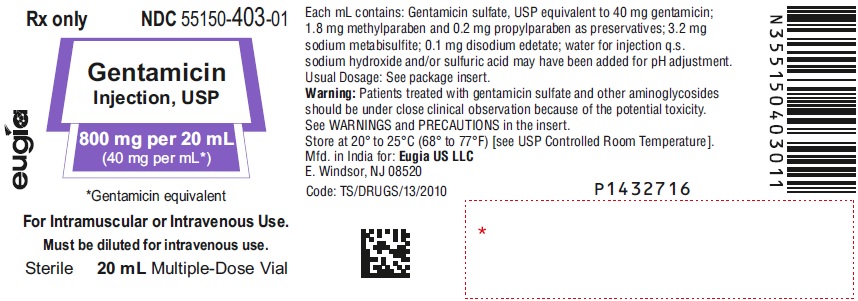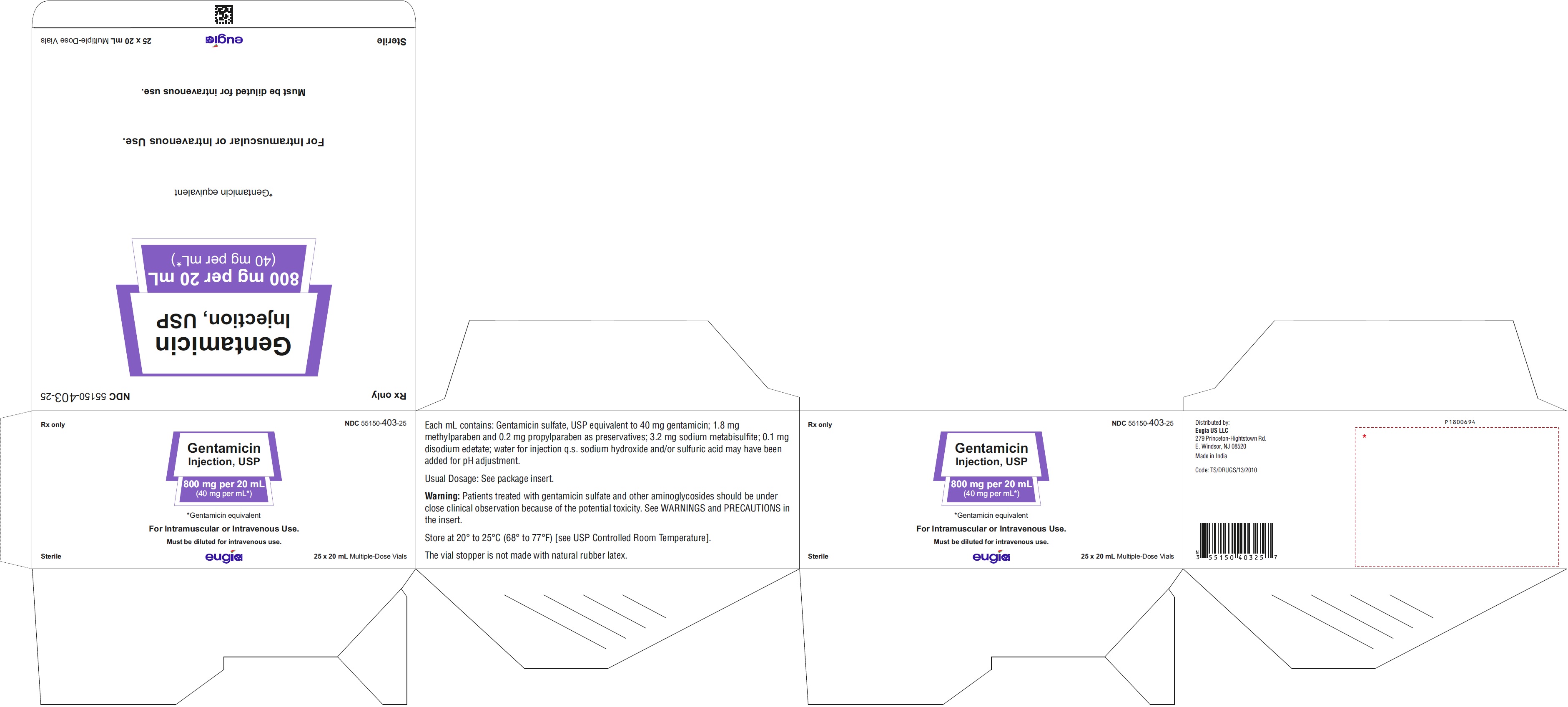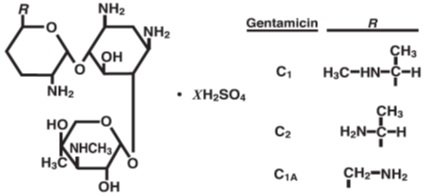 DRUG LABEL: Gentamicin
NDC: 55150-402 | Form: INJECTION, SOLUTION
Manufacturer: Eugia US LLC
Category: prescription | Type: Human Prescription Drug Label
Date: 20260129

ACTIVE INGREDIENTS: GENTAMICIN SULFATE 40 mg/1 mL
INACTIVE INGREDIENTS: EDETATE DISODIUM; PROPYLPARABEN; METHYLPARABEN; SODIUM METABISULFITE; SODIUM HYDROXIDE; SULFURIC ACID; WATER

Gentamicin Injection, USP

To reduce the development of drug-resistant bacteria and maintain the effectiveness of gentamicin injection and other antibacterial drugs, gentamicin injection should be used only to treat or prevent infections that are proven or strongly suspected to be caused by bacteria.

BOXED WARNINGS

Patients treated with aminoglycosides should be under close clinical observation because of the potential toxicity associated with their use.
As with other aminoglycosides, gentamicin injection is potentially nephrotoxic. The risk of nephrotoxicity is greater in patients with impaired renal function and in those who receive high dosage of prolonged therapy.
Neurotoxicity manifested by ototoxicity, both vestibular and auditory, can occur in patients treated with gentamicin, primarily in those with pre-existing renal damage and in patients with normal renal function treated with higher doses and/or for longer periods than recommended. Aminoglycoside-induced ototoxicity is usually irreversible. Other manifestations of neurotoxicity may include numbness, skin tingling, muscle twitching and convulsions.
Renal and eighth cranial nerve function should be closely monitored, especially in patients with known or suspected reduced renal function at onset of therapy and also in those whose renal function is initially normal but who develop signs of renal dysfunction during therapy. Urine should be examined for decreased specific gravity, increased excretion of protein and the presence of cells or casts. Blood urea nitrogen (BUN), serum creatinine or creatinine clearance should be determined periodically. When feasible, it is recommended that serial audiograms be obtained in patients old enough to be tested, particularly high-risk patients. Evidence of ototoxicity (dizziness, vertigo, tinnitus, roaring in the ears or hearing loss) or nephrotoxicity requires dosage adjustment or discontinuance of the drug. As with the other aminoglycosides, on rare occasions changes in renal and eighth cranial nerve function may not become manifest until soon after completion of therapy.
Serum concentrations of aminoglycosides should be monitored when feasible to assure adequate levels and to avoid potentially toxic levels. When monitoring gentamicin peak concentrations, dosage should be adjusted so that prolonged levels above 12 mcg/mL are avoided. When monitoring gentamicin trough concentrations, dosage should be adjusted so that levels above 2 mcg/mL are avoided. Excessive peak and/or trough serum concentrations of aminoglycosides may increase the risk of renal and eighth cranial nerve toxicity.
In the event of overdosage or toxic reactions, hemodialysis may aid in the removal of gentamicin from the blood, especially if renal function is, or becomes, compromised. The rate of removal of gentamicin is considerably lower by peritoneal dialysis than it is by hemodialysis.
In the newborn infant, exchange transfusions may also be considered.
Concurrent and/or sequential systemic or topical use of other potentially neurotoxic and/or nephrotoxic drugs, such as cisplatin, cephaloridine, kanamycin, amikacin, neomycin, polymyxin B, colistin, paromomycin, streptomycin, tobramycin, vancomycin and viomycin, should be avoided. Other factors which may increase patient risk of toxicity are advanced age and dehydration.
The concurrent use of gentamicin with potent diuretics, such as ethacrynic acid or furosemide, should be avoided, since certain diuretics by themselves may cause ototoxicity. In addition, when administered intravenously, diuretics may enhance aminoglycoside toxicity by altering the antibiotic concentration in serum and tissue.
Aminoglycosides can cause fetal harm when administered to a pregnant woman (see WARNINGS section).

DESCRIPTION:

Gentamicin sulfate, USP a water-soluble antibiotic of the aminoglycoside group, is derived by the growth of Micromonospora purpurea, an actinomycete.
It has the following structural formula.
Gentamicin injection, USP is a sterile, nonpyrogenic, aqueous solution for parenteral administration.
Each mL contains: Gentamicin sulfate, USP equivalent to 40 mg gentamicin, methylparaben 1.8 mg and propylparaben 0.2 mg as preservatives, sodium metabisulfite 3.2 mg and edetate disodium 0.1 mg, water for injection q.s. sodium hydroxide and/or sulfuric acid may have been added for pH adjustment.

CLINICAL PHARMACOLOGY:

After intramuscular (IM) administration of gentamicin sulfate, peak serum concentrations usually occur between 30 and 60 minutes and serum levels are measurable for six to eight hours. When gentamicin is administered by intravenous (IV) infusion over a two-hour period, the serum concentrations are similar to those obtained by intramuscular administration.
In patients with normal renal function, peak serum concentrations of gentamicin (mcg/mL) are usually up to four times the single intramuscular dose (mg/kg); for example, a 1 mg/kg injection in adults may be expected to result in a peak serum concentration up to 4 mcg/mL; a 1.5 mg/kg dose may produce levels up to 6 mcg/mL. While some variation is to be expected due to a number of variables such as age, body temperature, surface area and physiologic differences, the individual patient given the same dose tends to have similar levels in repeated determinations. Gentamicin administered at 1 mg/kg every eight hours for the usual 7 to 10 day treatment period to patients with normal renal function does not accumulate in the serum.
Gentamicin, like all aminoglycosides, may accumulate in the serum and tissues of patients treated with higher doses and/or for prolonged periods, particularly in the presence of impaired renal function. In adult patients, treatment with gentamicin dosages of 4 mg/kg/day or higher for 7 to 10 days may result in a slight, progressive rise in both peak and trough concentrations. In patients with impaired renal function, gentamicin is cleared from the body more slowly than in patients with normal renal function. The more severe the impairment, the slower the clearance. (Dosage must be adjusted.)
Since gentamicin is distributed in extra-cellular fluid, peak serum concentrations may be lower than usual in adult patients who have a large volume of this fluid. Serum concentrations of gentamicin in febrile patients may be lower than those in afebrile patients given the same dose. When body temperature returns to normal, serum concentrations of the drug may rise. Febrile and anemic states may be associated with a shorter than usual serum half-life. (Dosage adjustment is usually not necessary.) In severely burned patients, the half-life may be significantly decreased and resulting serum concentrations may be lower than anticipated from the mg/kg dose.
Protein binding studies have indicated that the degree of gentamicin binding is low; depending upon the methods used for testing, this may be between 0 and 30%.
After initial administration to patients with normal renal function, generally 70% or more of the gentamicin dose is recoverable in the urine in 24 hours; concentrations in urine above 100 mcg/mL may be achieved. Little, if any, metabolic transformation occurs; the drug is excreted principally by glomerular filtration. After several days of treatment, the amount of gentamicin excreted in the urine approaches the daily dose administered. As with other aminoglycosides, a small amount of the gentamicin dose may be retained in the tissues, especially in the kidneys. Minute quantities of aminoglycosides have been detected in the urine weeks after drug administration was discontinued. Renal clearance of gentamicin is similar to that of endogenous creatinine.
In patients with marked impairment of renal function, there is a decrease in the concentration of aminoglycosides in urine and in their penetration into defective renal parenchyma. This decreased drug excretion, together with the potential nephrotoxicity of aminoglycosides, should be considered when treating such patients who have urinary tract infections.
Probenecid does not affect renal tubular transport of gentamicin.
The endogenous creatinine clearance rate and the serum creatinine level have a high correlation with the half-life of gentamicin in serum. Results of these tests may serve as guides for adjusting dosage in patients with renal impairment (see DOSAGE AND ADMINISTRATION).
Following parenteral administration, gentamicin can be detected in serum, lymph, tissues, sputum and in pleural, synovial and peritoneal fluids. Concentrations in renal cortex sometimes may be eight times higher than the usual serum levels. Concentrations in bile, in general, have been low and have suggested minimal biliary excretion. Gentamicin crosses the peritoneal as well as the placental membranes. Since aminoglycosides diffuse poorly into the subarachnoid space after parenteral administration, concentrations of gentamicin in cerebrospinal fluid are often low and dependent upon dose, rate of penetration and degree of meningeal inflammation. There is minimal penetration of gentamicin into ocular tissues following intramuscular or intravenous administration.
Microbiology
Mechanism of Action
Gentamicin, an aminoglycoside, binds to the prokaryotic ribosome, inhibiting protein synthesis in susceptible bacteria. It is bactericidal in vitro against Gram-positive and Gram-negative bacteria.
Mechanism of Resistance
Bacterial resistance to gentamicin is generally developed slowly. Bacteria resistant to one aminoglycoside may be resistant to one or more other aminoglycosides. The following bacteria are usually resistant to the aminoglycosides, including gentamicin: most streptococcal species (including Streptococcus pneumoniae and the Group D streptococci), most enterococcal species (including Enterococcus faecalis, E. faecium, and E. durans), and anaerobic organisms, such as Bacteroides species and Clostridium species.
Aminoglycosides are known to be not effective against Salmonella and Shigella species in patients. Therefore, in vitro susceptibility test results should not be reported.
Interactions with Other Antimicrobials
In vitro studies show that an aminoglycoside combined with an antibiotic that interferes with cell wall synthesis may act synergistically against some enterococcal strains. The combination of gentamicin and penicillin G has a synergistic bactericidal effect against strains of Enterococcus faecalis, E. faecium and E. durans. An enhanced killing effect against many of these strains has also been shown in vitro with combinations of gentamicin and ampicillin, carbenicillin, nafcillin or oxacillin.
The combined effect of gentamicin and carbenicillin is synergistic for many strains of Pseudomonas aeruginosa. In vitro synergism against other Gram-negative organisms has been shown with combinations of gentamicin and cephalosporins.
Gentamicin may be active against clinical isolates of bacteria resistant to other aminoglycosides.
Antibacterial Activity
Gentamicin has been shown to be active against most of the following bacteria, both in vitro and in clinical infections (see INDICATIONS AND USAGE).
Gram-Positive Bacteria
Staphylococcus species
Gram-Negative Bacteria
Citrobacter species
Enterobacter species
Escherichia coli
Klebsiella species
Proteus species
Serratia species
Pseudomonas aeruginosa
Susceptibility Testing
For specific information regarding susceptibility test interpretive criteria and associated test methods and quality control standards recognized by FDA for this drug, please see: https://www.fda.gov/STIC.

INDICATIONS AND USAGE:

To reduce the development of drug-resistant bacteria and maintain the effectiveness of gentamicin injection and other antibacterial drugs, gentamicin injection should be used only to treat or prevent infections that are proven or strongly suspected to be caused by susceptible bacteria. When culture and susceptibility information are available, they should be considered in selecting or modifying antibacterial therapy. In the absence of such data, local epidemiology and susceptibility patterns may contribute to the empiric selection of therapy.
Gentamicin injection is indicated in the treatment of serious infections caused by susceptible strains of the following microorganisms: Pseudomonas aeruginosa, Proteus species (indole-positive and indole-negative), Escherichia coli, Klebsiella-Enterobacter-Serratia species, Citrobacter species and Staphylococcus species (coagulase-positive and coagulase-negative).
Clinical studies have shown gentamicin injection to be effective in bacterial neonatal sepsis; bacterial septicemia and serious bacterial infections of the central nervous system (meningitis), urinary tract, respiratory tract, gastrointestinal tract (including peritonitis), skin, bone and soft tissue (including burns). Aminoglycosides, including gentamicin, are not indicated in uncomplicated initial episodes of urinary tract infections unless the causative organisms are susceptible to these antibiotics and are not susceptible to antibiotics having less potential for toxicity.
Specimens for bacterial culture should be obtained to isolate and identify causative organisms and to determine their susceptibility to gentamicin.
Gentamicin injection may be considered as initial therapy in suspected or confirmed gram-negative infections, and therapy may be instituted before obtaining results of susceptibility testing. The decision to continue therapy with this drug should be based on the results of susceptibility tests, the severity of the infection and the important additional concepts contained in the BOXED WARNINGS. If the causative organisms are resistant to gentamicin, other appropriate therapy should be instituted.
In serious infections when the causative organisms are unknown, gentamicin injection may be administered as initial therapy in conjunction with a penicillin-type or cephalosporin-type drug before obtaining results of susceptibility testing. If anaerobic organisms are suspected as etiologic agents, consideration should be given to using other suitable antimicrobial therapy in conjunction with gentamicin. Following identification of the organism and its susceptibility, appropriate antibiotic therapy should then be continued.
Gentamicin injection has been used effectively in combination with carbenicillin for the treatment of life-threatening infections caused by Pseudomonas aeruginosa. It has also been found effective when used in conjunction with a penicillin-type drug for treatment of endocarditis caused by group D streptococci.
Gentamicin injection has also been shown to be effective in the treatment of serious staphylococcal infections. While not the antibiotic of first choice, gentamicin injection may be considered when penicillins or other less potentially toxic drugs are contraindicated and bacterial susceptibility tests and clinical judgment indicate its use. It may also be considered in mixed infections caused by susceptible strains of staphylococci and gram-negative organisms.
In the neonate with suspected bacterial sepsis or staphylococcal pneumonia, a penicillin-type drug is also usually indicated as concomitant therapy with gentamicin.

CONTRAINDICATIONS:

Hypersensitivity to gentamicin is a contraindication to its use. A history of hypersensitivity or serious toxic reactions to other aminoglycosides may contraindicate use of gentamicin because of the known cross-sensitivity of patients to drugs in this class.

WARNINGS:

(See BOXED WARNINGS.)
Contains sodium metabisulfite, a sulfite that may cause allergic-type reactions including anaphylactic symptoms and life-threatening or less severe asthmatic episodes in certain susceptible people. The overall prevalence of sulfite sensitivity in the general population is unknown and probably low. Sulfite sensitivity is seen more frequently in asthmatic than in non-asthmatic people.
Aminoglycosides can cause fetal harm when administered to a pregnant woman. Aminoglycoside antibiotics cross the placenta, and there have been several reports of total irreversible bilateral congenital deafness in children whose mothers received streptomycin during pregnancy. Serious side effects to mother, fetus or newborn have not been reported in the treatment of pregnant women with other aminoglycosides. Animal reproduction studies conducted on rats and rabbits did not reveal evidence of impaired fertility or harm to the fetus due to gentamicin sulfate.

It is not known whether gentamicin sulfate can cause fetal harm when administered to a pregnant woman or can affect reproduction capacity. If gentamicin is used during pregnancy or if the patient becomes pregnant while taking gentamicin, she should be apprised of the potential hazard to the fetus.

Risk of Ototoxicity Due to Mitochondrial DNA Variants
Cases of ototoxicity with aminoglycosides have been observed in patients with certain variants in the mitochondrially encoded 12S rRNA gene (MT-RNR1), particularly the m.1555A>G variant. Ototoxicity occurred in some patients even when their aminoglycoside serum levels were within the recommended range. Mitochondrial DNA variants are present in less than 1% of the general US population, and the proportion of the variant carriers who may develop ototoxicity as well as the severity of ototoxicity is unknown. In case of known maternal history of ototoxicity due to aminoglycoside use or a known mitochondrial DNA variant in the patient, consider alternative treatments other than aminoglycosides unless the increased risk of permanent hearing loss is outweighed by the severity of infection and lack of safe and effective alternative therapies.

PRECAUTIONS:

General
Prescribing gentamicin injection in the absence of a proven or strongly suspected bacterial infection or a prophylactic indication is unlikely to provide benefit to the patient and increases the risk of the development of drug-resistant bacteria.
Neurotoxic and nephrotoxic antibiotics may be almost completely absorbed from body surfaces (except urinary bladder) after local irrigation and after topical application during surgical procedures. The potential toxic effects of antibiotics administered in this fashion (neuromuscular blockage, respiratory paralysis, oto- and nephrotoxicity) should be considered (see BOXED WARNINGS).
Increased nephrotoxicity has been reported following concomitant administration of aminoglycoside antibiotics and cephalosporins.
Neuromuscular blockade and respiratory paralysis have been reported in the cat receiving high doses (40 mg/kg) of gentamicin. The possibility of these phenomena occurring in man should be considered if aminoglycosides are administered by any route to patients receiving anesthetics, or to patients receiving neuromuscular blocking agents, such as succinylcholine, tubocurarine or decamethonium, or in patients receiving massive transfusions of citrate-anticoagulated blood. If neuromuscular blockade occurs, calcium salts may reverse it.
Aminoglycosides should be used with caution in patients with neuromuscular disorders, such as myasthenia gravis or parkinsonism, since these drugs may aggravate muscle weakness because of their potential curare-like effects on the neuromuscular junction. During or following gentamicin therapy, paresthesias, tetany, positive Chvostek and Trousseau signs and mental confusion have been described in patients with hypomagnesemia, hypocalcemia and hypokalemia. When this has occurred in infants, tetany and muscle weakness has been described. Both adults and infants required corrective electrolyte therapy.
Elderly patients may have reduced renal function which may not be evident in the results of routine screening tests such as BUN or serum creatinine. A creatinine clearance determination may be more useful. Monitoring of renal function during treatment with gentamicin, as with other aminoglycosides, is particularly important in such patients. A Fanconi-like syndrome, with amino-aciduria and metabolic acidosis has been reported in some adults and infants being given gentamicin injections.
Cross-allergenicity among aminoglycosides has been demonstrated.
Patients should be well hydrated during treatment.
Although the in vitro mixing of gentamicin and carbenicillin results in a rapid and significant inactivation of gentamicin, this interaction has not been demonstrated in patients with normal renal function who received both drugs by different routes of administration. A reduction in gentamicin serum half-life has been reported in patients with severe renal impairment receiving carbenicillin concomitantly with gentamicin.
Treatment with gentamicin may result in overgrowth of non-susceptible organisms. If this occurs, appropriate therapy is indicated.
See BOXED WARNINGS regarding concurrent use of potent diuretics and regarding concurrent and/or sequential use of other neurotoxic and/or for other essential information.
Information for Patients
Patients should be counseled that antibacterial drugs including gentamicin injection should only be used to treat bacterial infections. They do not treat viral infections (e.g., the common cold). When gentamicin injection is prescribed to treat a bacterial infection, patients should be told that although it is common to feel better early in the course of therapy, the medication should be taken exactly as directed. Skipping doses or not completing the full course of therapy may (1) decrease the effectiveness of the immediate treatment and (2) increase the likelihood that bacteria will develop resistance and will not be treatable by gentamicin injection or other antibacterial drugs in the future.
See WARNINGS section.

ADVERSE REACTIONS:

Nephrotoxicity
Adverse renal effects, as demonstrated by the presence of casts, cells or protein in the urine or by rising BUN, NPN, serum creatinine or oliguria, have been reported. They occur more frequently in patients with a history of renal impairment (especially if dialysis is required) and in patients treated for longer periods or with larger doses than recommended.
Neurotoxicity
Serious adverse effects on both vestibular and auditory branches of the eighth nerve have been reported, primarily in patients with renal impairment (especially if hemodialysis is required) and in patients on high doses and/or prolonged therapy. Symptoms include dizziness, vertigo, tinnitus, roaring in the ears and also hearing loss, which, as with the other aminoglycosides, may be irreversible. Hearing loss is usually manifested initially by diminution of high-tone acuity. Other factors which may increase the risk of toxicity include excessive dosage, dehydration and previous exposure to other ototoxic drugs.
Peripheral neuropathy or encephalopathy, including numbness, skin tingling, muscle twitching, convulsions and a myasthenia gravis-like syndrome have been reported.
Note: The risk of toxic reactions is low in patients with normal renal function who did not receive gentamicin sulfate at higher doses or for longer periods of time than recommended.
Other reported adverse reactions possibly related to gentamicin include: respiratory depression, lethargy, confusion, depression, visual disturbances, decreased appetite, weight loss and hypotension and hypertension; rash, itching, urticaria, generalized burning, laryngeal edema, anaphylactoid reactions, fever and headache; nausea, vomiting, increased salivation and stomatitis; purpura, pseudotumor cerebri, acute organic brain syndrome, pulmonary fibrosis, alopecia, joint pain, transient hepatomegaly and splenomegaly.
Laboratory abnormalities possibly related to gentamicin include: increased levels of serum transaminase (SGOT, SGPT), serum LDH and bilirubin; decreased serum calcium, magnesium, sodium and potassium; anemia, leukopenia, granulocytopenia, transient agranulocytosis, eosinophilia, increased and decreased reticulocyte counts and thrombocytopenia. While clinical laboratory test abnormalities may be isolated findings, they may also be associated with clinically related signs and symptoms. For example, tetany and muscle weakness may be associated with hypomagnesemia, hypocalcemia and hypokalemia.
While the local tolerance of gentamicin sulfate is generally excellent, there has been an occasional report of pain at the injection site. Subcutaneous atrophy or fat necrosis suggesting local irritation has been reported rarely.
To report SUSPECTED ADVERSE REACTIONS, contact Eugia US LLC at 1-866-850-2876 or FDA at 1-800-FDA-1088 or www.fda.gov/medwatch.

OVERDOSAGE:

In the event of overdosage or toxic reactions, hemodialysis may aid in the removal of gentamicin from the blood, especially if renal function is, or becomes, compromised. The rate of removal of gentamicin is considerably lower by peritoneal dialysis than it is by hemodialysis.

DOSAGE AND ADMINISTRATION:

Gentamicin injection may be given intramuscularly or intravenously. The patient’s pretreatment body weight should be obtained for calculation of correct dosage. The dosage of aminoglycosides in obese patients should be based on an estimate of the lean body mass. It is desirable to limit the duration of treatment with aminoglycosides to short term.

Patients with Normal Renal Function

Adults

The recommended dosage of gentamicin injection for patients with serious infections and normal renal function is 3 mg/kg/day, administered in three equal doses every eight hours (Table 3).

For patients with life-threatening infections, dosages up to 5 mg/kg/day may be administered in three or four equal doses. This dosage should be reduced to 3 mg/kg/day as soon as clinically indicated (Table 3).

It is desirable to measure both peak and trough serum concentrations of gentamicin to determine the adequacy and safety of the dosage. When such measurements are feasible, they should be carried out periodically during therapy to assure adequate but not excessive drug levels. For example, the peak concentration (at 30 to 60 minutes after intramuscular injection) is expected to be in the range of 4 to 6 mcg/mL. When monitoring peak concentrations after intramuscular or intravenous administration, dosage should be adjusted so that prolonged levels above 12 mcg/mL are avoided. When monitoring trough concentrations (just prior to the next dose), dosage should be adjusted so that levels above 2 mcg/mL are avoided. Determination of the adequacy of a serum level for a particular patient must take into consideration the susceptibility of the causative organism, the severity of the infection and the status of the patient’s host-defense mechanisms.

In patients with extensive burns, altered pharmacokinetics may result in reduced serum concentrations of aminoglycosides. In such patients treated with gentamicin, measurement of serum concentrations is recommended as a basis for dosage adjustment.

Table 3 Dosage Schedule Guide for Adults with Normal Renal Function
(Dosage at Eight-Hour Intervals)
40 mg per mL
Patient’s Weight* kg (lb) |  | Usual Dose for Serious Infections 1 mg/kg q8h (3 mg/kg/day) |  | Dose for Life-Threatening Infections (Reduce As Soon As Clinically Indicated) 1.7 mg/kg q8h** (5 mg/kg/day)
 |  | mg/dose | mL/dose | mg/dose | mL/dose
 |  | q8h |  | q8h
40 | (88) | 40 | 1 | 66 | 1.6
45 | (99) | 45 | 1.1 | 75 | 1.9
50 | (110) | 50 | 1.25 | 83 | 2.1
55 | (121) | 55 | 1.4 | 91 | 2.25
60 | (132) | 60 | 1.5 | 100 | 2.5
65 | (143) | 65 | 1.6 | 108 | 2.7
70 | (154) | 70 | 1.75 | 116 | 2.9
75 | (165) | 75 | 1.9 | 125 | 3.1
80 | (176) | 80 | 2 | 133 | 3.3
85 | (187) | 85 | 2.1 | 141 | 3.5
90 | (198) | 90 | 2.25 | 150 | 3.75
95 | (209) | 95 | 2.4 | 158 | 4
100 | (220) | 100 | 2.5 | 166 | 4.2

* The dosage of aminoglycosides in obese patients should be based on an estimate of the lean body mass.

** for q6h schedules, dosage should be recalculated.

Children

6 to 7.5 mg/kg/day (2 to 2.5 mg/kg administered every eight hours).

Infants and Neonates

7.5 mg/kg/day (2.5 mg/kg administered every eight hours).

Premature or Full-Term Neonates One Week of Age or Less

5 mg/kg/day (2.5 mg/kg administered every 12 hours).

For further information concerning the use of gentamicin in infants and children, see gentamicin injection (pediatric) product information.

The usual duration of treatment for all patients is 7 to 10 days. In difficult and complicated infections, a longer course of therapy may be necessary. In such cases monitoring of renal, auditory and vestibular functions is recommended, since toxicity is more apt to occur with treatment extended for more than 10 days. Dosage should be reduced if clinically indicated.

For Intravenous Administration

The intravenous administration of gentamicin may be particularly useful for treating patients with bacterial septicemia or those in shock. It may also be the preferred route of administration for some patients with congestive heart failure, hematologic disorders, severe burns or those with reduced muscle mass. For intermittent intravenous administration in adults, a single-dose of gentamicin injection may be diluted in 50 to 200 mL of sterile isotonic saline solution or in a sterile solution of dextrose 5% in water; in infants and children, the volume of diluent should be less. The solution may be infused over a period of one-half to two hours.

The recommended dosage for intramuscular and intravenous administration is identical.

Gentamicin injection should not be physically premixed with other drugs, but should be administered separately in accordance with the recommended route of administration and dosage schedule.

Patients with Impaired Renal Function

Dosage must be adjusted in patients with impaired renal function to assure therapeutically adequate, but not excessive blood levels. Whenever possible serum concentration of gentamicin should be monitored. One method of dosage adjustment is to increase the interval between administration of the usual doses. Since the serum creatinine concentration has a high correlation with the serum half-life of gentamicin, this laboratory test may provide guidance for adjustment of the interval between doses. The interval between doses (in hours) may be approximated by multiplying the serum creatinine level (mg/100 mL) by 8. For example, a patient weighing 60 kg with a serum creatinine level of 2 mg/100 mL could be given 60 mg (1 mg/kg) every 16 hours (2 x 8).

In patients with serious systemic infections and renal impairment, it may be desirable to administer the antibiotic more frequently but in reduced dosage. In such patients, serum concentrations of gentamicin should be measured so that adequate but not excessive levels result. A peak and trough concentration measured intermittently during therapy will provide optimal guidance for adjusting dosage. After the usual initial dose, a rough guide for determining reduced dosage at eight-hour intervals is to divide the normally recommended dose by the serum creatinine level (Table 4). For example, after an initial dose of 60 mg (1 mg/kg), a patient weighing 60 kg with a serum creatinine level of 2 mg/100 mL could be given 30 mg every eight hours (60 ÷ 2). It should be noted that the status of renal function may be changing over the course of the infectious process.

It is important to recognize that deteriorating renal function may require a greater reduction in dosage than that specified in the above guidelines for patients with stable renal impairment.

Table 4 Dosage Adjustment Guide for Patients with Renal Impairment
(Dosage at Eight-Hour Intervals After the Usual Initial Dose)
Serum Creatinine (mg %) | Approximate Creatinine Clearance Rate (mL/min/1.73m^2) | Percent of Usual Doses Shown Above
≤ 1 | > 100 | 100
1.1 to 1.3 | 70 to 100 | 80
1.4 to 1.6 | 55 to 70 | 65
1.7 to 1.9 | 45 to 55 | 55
2 to 2.2 | 40 to 45 | 50
2.3 to 2.5 | 35 to 40 | 40
2.6 to 3 | 30 to 35 | 35
3.1 to 3.5 | 25 to 30 | 30
3.6 to 4 | 20 to 25 | 25
4.1 to 5.1 | 15 to 20 | 20
5.2 to 6.6 | 10 to 15 | 15
6.7 to 8 | < 10 | 10

In adults with renal failure undergoing hemodialysis, the amount of gentamicin removed from the blood may vary depending upon several factors including the dialysis method used. An eight-hour hemodialysis may reduce serum concentrations of gentamicin by approximately 50%. The recommended dosage at the end of each dialysis period is 1 to 1.7 mg/kg depending upon the severity of the infection. In children, a dose of 2 mg/kg may be administered.

The above dosage schedules are not intended as rigid recommendations but are provided as guides to dosage when measurement of gentamicin serum level is not feasible.

A variety of methods are available to measure gentamicin concentrations in body fluids; these include microbiologic, enzymatic and radioimmunoassay techniques.

Parenteral drug products should be inspected visually for particulate matter and discoloration prior to administration, whenever solution and container permit.

HOW SUPPLIED:

Gentamicin injection, USP, is a sterile, clear colorless to slightly yellow color solution containing gentamicin 40 mg/ml and is supplied as follows:
80 mg per 2 mL (40 mg/mL)
2 mL fill in a 2 mL Multiple-Dose Vials
Packaged in a Carton of 25 NDC 55150-402-25
800 mg per 20 mL (40 mg/mL)
20 mL fill in a 20 mL Multiple-Dose Vials
Packaged in a Carton of 25 NDC 55150-403-25
Store at 20° to 25°C (68° to 77°F) [see USP Controlled Room Temperature].
The vial stopper is not made with natural rubber latex.
Distributed by:
Eugia US LLC
279 Princeton-Hightstown Rd.
E. Windsor, NJ 08520
Manufactured by:
Eugia Pharma Specialities Limited
Hyderabad - 500032
India
Revised: December 2023

PACKAGE LABEL-PRINCIPAL DISPLAY PANEL-80 mg per 2 mL (40 mg per mL) - Container Label

Rx only NDC 55150-402-01
Gentamicin
Injection, USP
80 mg per 2 mL
(40 mg per mL*)
*Gentamicin equivalent
Sterile 2 mL Multiple-Dose Vial

PACKAGE LABEL-PRINCIPAL DISPLAY PANEL-80 mg per 2 mL (40 mg per mL) - Container-Carton

Rx only NDC 55150-402-25
Gentamicin
Injection, USP
80 mg per 2 mL
(40 mg per mL*)
*Gentamicin equivalent
For Intramuscular or Intravenous Use.
Must be Diluted for intravenous use.
Sterile eugia 25 x 2 mL Multiple-Dose Vials

PACKAGE LABEL-PRINCIPAL DISPLAY PANEL-800 mg per 20 mL (40 mg per mL) - Container Label

Rx only NDC 55150-403-01
Gentamicin
Injection, USP
800 mg per 20 mL
(40 mg per mL*)
*Gentamicin equivalent
For Intramuscular or Intravenous Use.
Must be diluted for intravenous use.
Sterile 20 mL Multiple-Dose Vial

PACKAGE LABEL-PRINCIPAL DISPLAY PANEL-800 mg per 20 mL (40 mg per mL) - Container-Carton

Rx only NDC 55150-403-25
Gentamicin
Injection, USP
800 mg per 20 mL
(40 mg per mL*)
*Gentamicin equivalent
For Intramuscular or Intravenous Use.
Must be diluted for intravenous use.
Sterile eugia 25 x 20 mL Multiple-Dose Vials